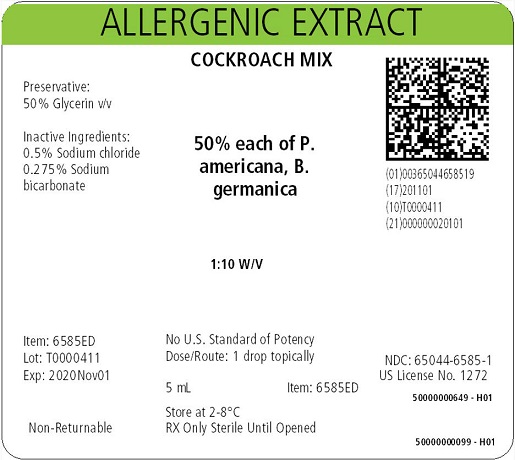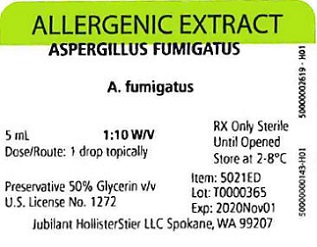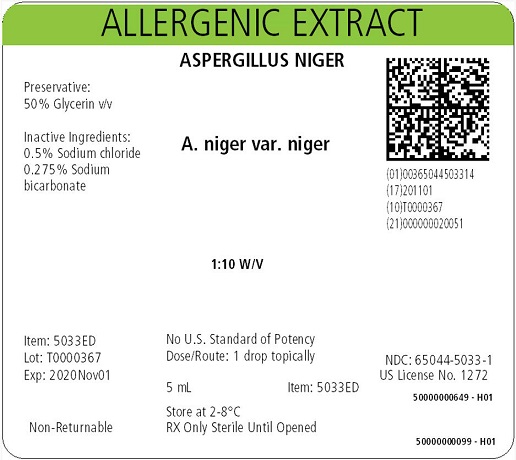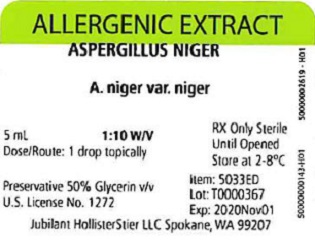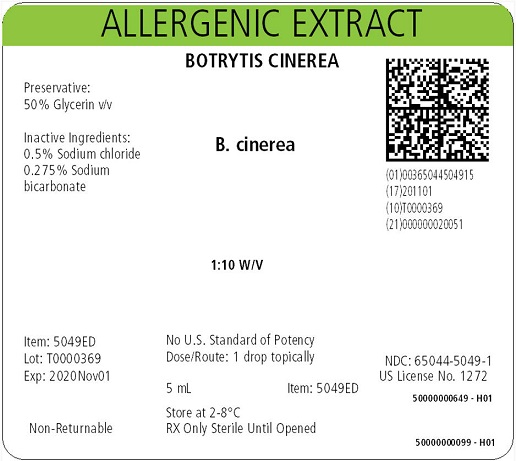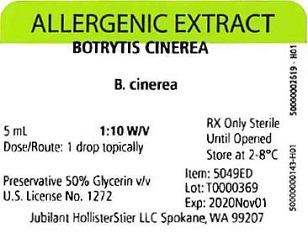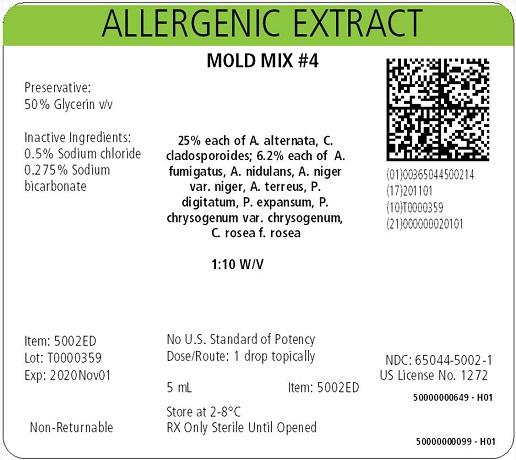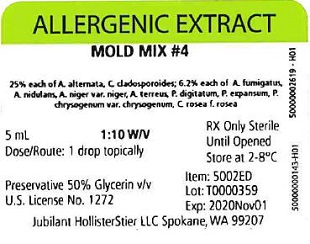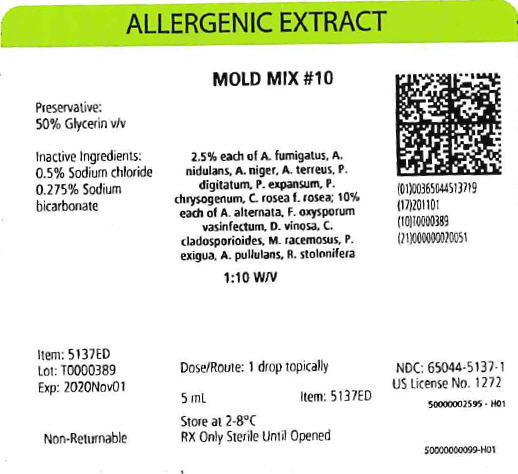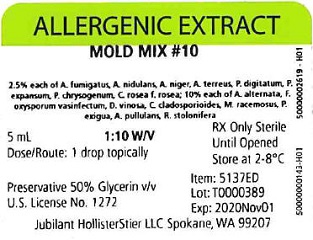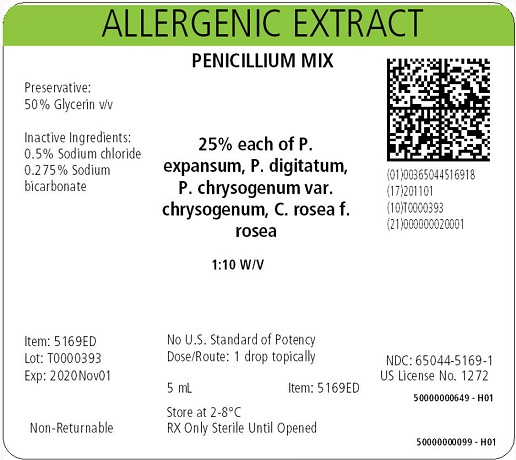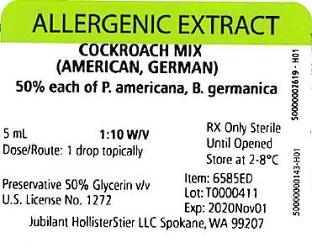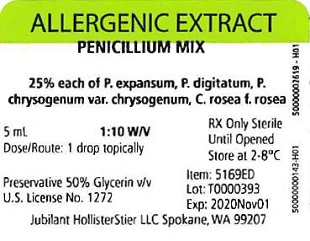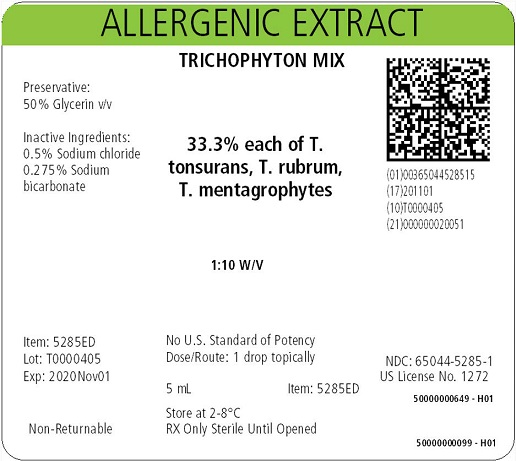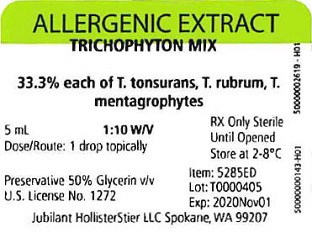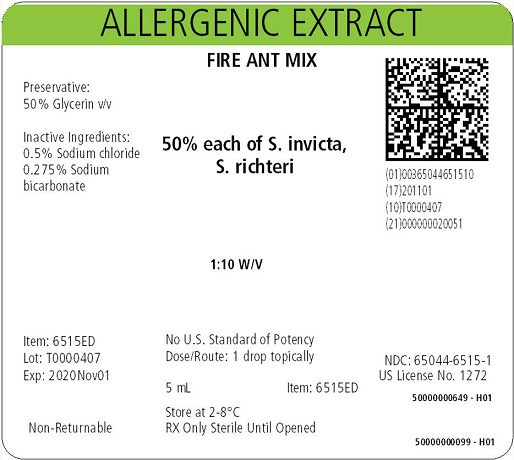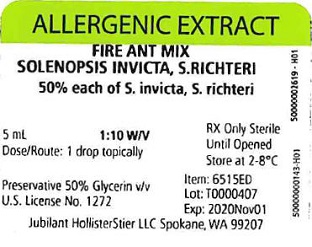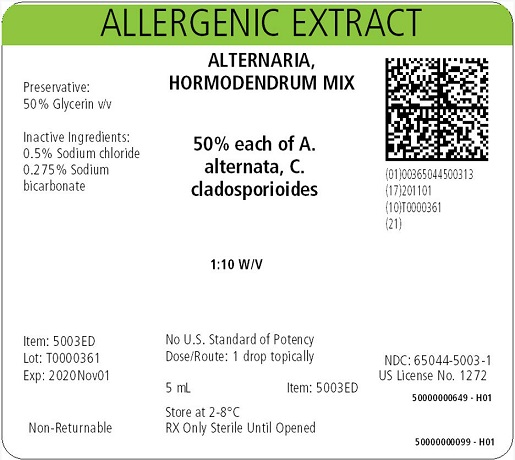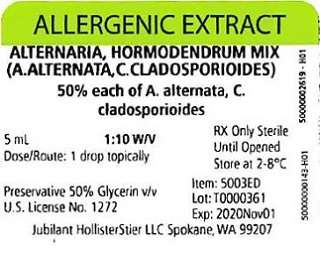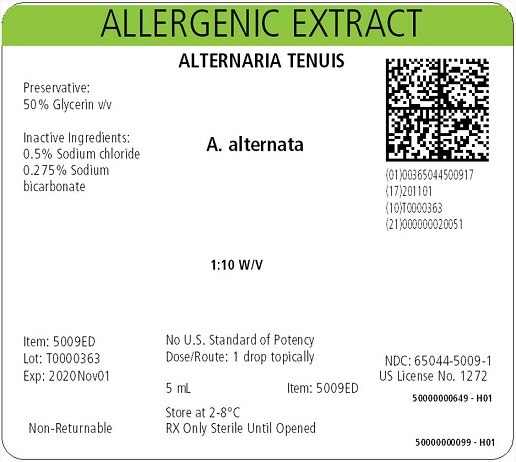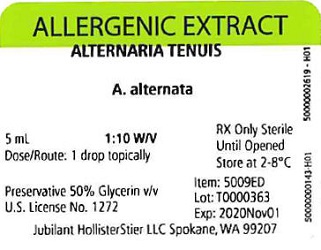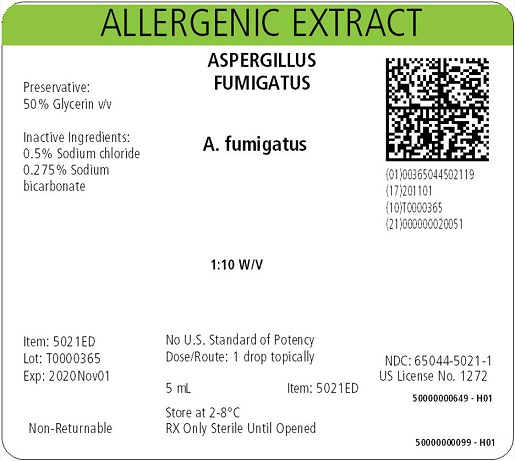 DRUG LABEL: Food - Plant Source, Yeast, Baker Saccharomyces cerevisiae
NDC: 65044-3714 | Form: INJECTION, SOLUTION
Manufacturer: Jubilant HollisterStier LLC
Category: other | Type: NON-STANDARDIZED ALLERGENIC LABEL
Date: 20200114

ACTIVE INGREDIENTS: YEAST 0.1 g/1 mL
INACTIVE INGREDIENTS: GLYCERIN; SODIUM CHLORIDE; SODIUM BICARBONATE

INSTRUCTIONS ALLERGENIC EXTRACTS FOR SCRATCH, PRICK OR PUNCTURE TESTING

WARNINGS

This product is intended for use only by licensed medical personnel experienced in administering allergenic extracts and trained to provide immediate emergency treatment in the event of a life-threatening reaction. Allergenic extracts may potentially elicit a severe life threatening systemic reaction, rarely resulting in death.7 Therefore, emergency measures and personnel trained in their use must be available immediately in the event of such a reaction. Patients should be instructed to recognize adverse reaction symptoms and cautioned to contact the physician's office if symptoms occur. Patients on non-selective beta blockers may be more reactive to allergens given for testing or treatment and may be unresponsive to the usual doses of epinephrine used to treat allergic reactions. This product should never be injected intravenously. Refer also to the WARNINGS, PRECAUTIONS, and ADVERSE REACTIONS Sections for further discussion.

DESCRIPTION

Sterile extracts for scratch, prick or puncture testing are supplied in dropper vials containing, in addition to the extract allergens and antigens, 50% (v/v) glycerin as preservative, 0.5% sodium chloride and 0.275% sodium bicarbonate. The strength of these extracts may be expressed in terms of

- Weight to Volume (w/v)
- Protein Nitrogen Units/mL (PNU/mL)
- Amb a 1 Units/mL (Amb a 1/mL)
- Allergy Units/mL (AU/mL)
- Bioequivalent Allergy Units/mL (BAU/mL)
- Concentrate

1. Weight to volume (w/v).
For regular extracts this describes the extraction ratio, i.e., the amount of crude allergen added to the extracting fluid. A 1:10 extract, therefore, indicates that the solution contains the extracted material from one gram of raw material added to each 10 mL of extracting fluid. The amount and composition of extracted materials will vary with the kind of antigen, the extracting fluid, duration of extraction, pH, temperature, and other variables. AP™ (acetone precipitated) extracts, if present, are prepared by reconstituting dry, allergenically active concentrates produced by precipitation process from extracts of raw materials. For those AP™ extracts labeled on a weight per volume (w/v) basis, the strength designation indicates the dry weight of finished (acetone) precipitate per volume of reconstituting fluid. For example, 1:50 (w/v) means that each gram of dry precipitate obtained from the original extract is reconstituted in 50 mL of solution.

2. Protein Nitrogen Units per mL (PNU/mL).
One protein nitrogen unit represents 0.00001 mg phosphotungstic acid-precipitable protein nitrogen dissolved in one mL of antigen extract. The PNU content of extracts of the same antigen may vary according to the method of measuring the PNU. Thus, the PNU content of extracts from different manufacturers is not comparable unless the PNU method is known to be the same and reproducible from lot to lot. Also, the amount of protein nitrogen extracted from an antigen is influenced by the same variables as the weight to volume extract. Allergenic materials make up a variable proportion of the total protein of an extract.

3. Amb a 1. Of the many allergens which have been purified and characterized from Short Ragweed (Amb a 1^12, Amb a 2^13, Ra3^14, Ra4(BPA-R)^15, Ra5^16, Ra6, Ra7, and Ra8^17, and cytochrome C^18), Amb a 1 (also known as Antigen E) is considered the most important and has been selected as the basis for standardization. Extracts of Short Ragweed containing Amb a 1 are diffused in agar against standard anti-serum to Amb a 1, and compared to the diffusion of standard Amb a 1 solutions. The amount of Amb a 1 is expressed as units of Amb a 1 per mL of extract.

If an extract is diluted with a diluent or other allergenic extracts, the Amb a 1 concentration must be determined by calculation.

4. Allergy Units per mL (AU/mL).
The potency of extracts labeled in Allergy Units per mL (AU/mL) is determined by in vitro comparison to a reference standard established by the Center for Biologics Evaluation and Research (CBER) of the Food and Drug Administration (FDA).

5. Bioequivalent Allergy Units per mL (BAU/mL).
When originally licensed, the Reference Preparations for standardized extracts were arbitrarily assigned 100,000 Allergy Units (AU)/mL. Subsequently, quantitative skin testing by the ID50EAL method 13 was used to determine that some Reference Preparations should be assigned 10,000 AU/mL, and others 100,000 AU/mL. To avoid possible confusion about this change in the method of allergy unit assignment, the nomenclature changed for standardized extracts whose allergy units are assigned based on quantitative skin testing, and such products are labeled in Bioequivalent Allergy Units (BAU)/mL. References labeled 10,000 BAU/mL can be diluted one to a half million fold, and references labeled 100,000 BAU/mL can be diluted one to 5 million fold and produce a sum of erythema diameter of 50 mm when Intradermal testing highly reactive subjects.

6. Concentrate.
Concentrate label terminology applies to allergenic extract mixtures, where the individual allergens being combined vary in strength or the designation of strength.

CLINICAL PHARMACOLOGY

Allergenic extracts for scratch, prick or puncture testing, used according to the DOSAGE AND ADMINISTRATION section, produce erythema or erythema and wheal reactions in patients with significant IgE-mediated sensitivity to the relevant allergen. This allergic inflammatory response, although not completely understood, is thought to begin with reaction of antigen with IgE on the surface of basophils or mast cells, which initiates a series of biochemical events resulting in the production of histamine and other mediators. These, in turn, produce the immediate-type "wheal and flare" skin reaction.

INDICATIONS & USAGE

Certain diagnostics carry labeling which states Allergenic Extract for Diagnostic Use Only. Data to support the therapeutic use of products labeled with this statement have not been established. 14
In addition to a carefully taken history, the use of glycerin-containing extracts in scratch, prick or puncture testing is an accepted method in the diagnosis of allergic conditions. 1, 2, 3 Extracts of all allergens do not produce equivalent results in scratch, prick or puncture tests. The intensity of the skin reactions produced will be determined by two factors: the degree of sensitivity of the patient, and the nature of the allergenic extract applied.
Scratch, prick or puncture tests are not as sensitive as the intradermal test, but are safer and cause less discomfort. They may, therefore, be the method of choice when a large number of tests are needed, or when testing the pediatric patient. In some cases, where the relatively insensitive scratch, prick or puncture tests are negative or do not confirm the allergic history, follow-up intradermal tests may be positive. However, ANTIGENS PRODUCING LARGE 3 to 4+ SCRATCH, PRICK OR PUNCTURE TESTS SHOULD NOT BE TESTED INTRADERMALLY.

CONTRAINDICATIONS

There are no known absolute contraindications to allergy skin testing. Patients with cardiovascular diseases or pulmonary diseases such as symptomatic asthma, and/or who are receiving cardiovascular drugs such as beta blockers, may be at higher risk for severe adverse reactions. These patients may also be more refractory to the normal anaphylaxis treatment regimen.

WARNINGS

Excessively large local reactions or systemic reactions are more likely to occur if the patient is skin tested shortly after exposure to large amounts of antigen to which s/he is sensitive. Use caution when skin testing patients during a season when pollen is present. Refer to boxed WARNINGS Section.

PRECAUTIONS

1. General

Always have injectable epinephrine and a tourniquet available when tests are being made. (See ADVERSE REACTIONS section.) Generally 50 to 60 scratch, prick or puncture tests can be applied safely at one sitting. Patients whose history suggests severe sensitivity should have only 5 to 10 tests applied at a time and these tests applied to the volar surface of one arm. These tests should not all be of the same type of antigen; that is, all grass pollens, all weed pollens, all danders, etc. One or two tests from several classes of antigens should be applied at a time. As soon as a large wheal begins to develop, wipe the antigen from it with a damp cotton sponge. After 10 minutes wipe off all the antigens with a damp cotton sponge, followed by a dry cotton sponge. Be careful not to wipe antigen from a positive reaction onto an adjacent test site.

2 Information for Patients

Patients should be instructed in the recognition of adverse reactions to diagnostic testing. Patients should be made to understand the importance of a 30 minute observation period, and be warned to return to the office promptly if symptoms occur after leaving.

3. Drug Interactions

Patients on non-selective beta blockers may be more reactive to allergens given for testing or treatment and may be unresponsive to the usual doses of epinephrine used to treat allergic reactions.6
Certain medications may lessen the skin test wheal and erythema responses elicited by allergens and histamine for varying time periods. Conventional antihistamines should be discontinued at least 5 days before skin testing. Long acting antihistamines should be discontinued for at least 3 weeks prior to skin testing.9 Topical steroids should be discontinued at the skin test site for at least 2-3 weeks before skin testing.9, 10 Tricyclic antidepressants such as Doxepin should be withheld for at least 7 days before skin testing.11 Topical local anesthetics may suppress the flare responses and should be
avoided in skin test sites.12

4. Carcinogenesis, mutagenesis, Impairment of Fertility

Long-term studies in animals have not been conducted with allergenic extracts to determine their potential for carcinogenicity, mutagenicity or impairment of fertility.

5. Pregnancy

4,5
Animal reproduction studies have not been conducted with allergenic extracts. It is also not known whether allergenic extracts can cause fetal harm when administered to a pregnant woman or can affect reproduction capacity. Allergenic extracts should be given to a pregnant woman only if clearly needed.

6. Nursing Mothers

There are no current studies on secretion of the allergenic extract components in human milk or effect on the nursing infant. Because many drugs are excreted in human milk, caution should be exercised when allergenic extracts are administered to a nursing woman.

7. Pediatric Use

Wheal sizes in response to allergen skin testing can be smaller in infants than in adults. The skin response to histamine parallels that for allergens; therefore, appropriate positive control skin tests should always be performed.1

8. Geriatric Use

Skin test wheal size decreases with age. The decrease in allergen-induced skin test reaction parallels that to histamine; therefore, appropriate positive skin test controls should always be performed.1

ADVERSE REACTIONS

1. Local Reactions
If a severe local reaction occurs during scratch, prick or puncture testing, WIPE OFF test antigen. Large, persistent local reactions or minor exacerbations of the patient's allergic symptoms may be treated by local cold applications and/or the use of oral antihistamines, but they should be considered a warning of possible severe systemic reactions.

2. Systemic Reactions
With careful attention to dosage and administration, such reactions occur infrequently, but it must be remembered that allergenic extracts are highly potent in sensitive individuals and OVERDOSE could result in anaphylactic symptoms. Therefore, it is imperative that physicians administering allergenic extracts understand and be prepared for the treatment of severe reactions.
Adverse reaction frequency data for allergenic extract administration for testing and treatment show that risk is low.7, 8
It cannot be overemphasized that, under certain unpredictable combinations of circumstances, anaphylactic shock is a possibility. Other possible systemic reaction symptoms include fainting, pallor, bradycardia, hypotension, angioedema, cough, wheezing, conjunctivitis, rhinitis and urticaria. If a systemic or anaphylactic reaction does occur, WIPE OFF test antigen, apply a tourniquet above the site of injection, if tests are performed on the arms, and inject the 1:1,000 epinephrine-hydrochloride intramuscularly or subcutaneously into the opposite arm. Loosen the tourniquet at least every 10 minutes. Do not obstruct arterial blood flow with the tourniquet.
EPINEPHRINE:
ADULT DOSAGE: 0.3 to 0.5 mL should be injected. Repeat in 5 to 10 minutes if necessary.
PEDIATRIC DOSAGE: The usual initial dose is 0.01 mg (mL) per kg body weight or 0.3 mg (mL) per square meter of body surface area. Suggested dosage for infants to 2 years of age is 0.05 mL to 0.1 mL; for children 2 to 6 years, 0.15 mL; and children 6 to 12 years, 0.2 mL. Single pediatric doses should not exceed 0.3 mg (mL). Doses may be repeated as frequently as every 20 minutes, depending on the severity of the condition and the response of the patient. After administration of epinephrine, profound shock or vasomotor collapse should be treated with intravenous fluids, and other appropriate drugs. Oxygen should be given by mask. Intravenous antihistamine, theophylline or corticosteroids may be used if necessary after adequate epinephrine and circulatory support have been given. Emergency resuscitation measures and personnel trained in their use should be available immediately in the event of a serious systemic or anaphylactic reaction not responsive to the above measures (Ref. J. Allergy Clin. Immunol. 77 (2): 271-273, 1986). Rarely are all of the above measures necessary; the tourniquet and epinephrine usually produce prompt responses. However, the physician should be prepared in advance for all contingencies. Promptness in beginning emergency treatment measures is of utmost importance.
3. Adverse Event Reporting
Report all adverse events to Jubilant HollisterStier LLC Customer Technical Services Department at 1 (800) 992-1120. A voluntary adverse event reporting system for health professionals is available through the FDA MEDWATCH program. Preprinted forms (FDA Form 3500) are available from the FDA by calling 1 (800) FDA-1088. Completed forms should be mailed to MEDWATCH, 5600 Fisher Lane, Rockville, MD 20852-9787 or Fax to: 1 (800) FDA-0178.

OVERDOSAGE

See ADVERSE REACTIONS Section.

DOSAGE & ADMINISTRATION

1. General
Parenteral Drug Products should be inspected visually for particulate matter and discoloration prior to administration, whenever solution and container permit.

2. Scratch, Prick or Puncture Testing Methods
There are two general methods of skin testing. (1) The skin is scarified first, and the extract is then applied. (2) A drop of extract is put onto the skin, and a prick or puncture is made through the drop. Avoid touching tip of dropper to skin. Either method is satisfactory, but the second requires that the instrument be cleansed between tests or that separate needles be used.

The extracts for scratch, prick or puncture testing are supplied in dropper vials and should be kept in a rack or box in rows of 10 vials corresponding to the rows of tests to be applied to the skin.

All skin tests should be validated by appropriate positive control tests (e.g., histamine) and negative control tests (e.g., Glycerin, Albumin Saline with Phenol (0.4%), or Buffered Saline with Phenol). The negative control test should be the same material as is used as a diluting fluid in the tested extracts. Diluting fluid is used in the same way as an active test extract.

Test sites should be examined at 15 and 30 minutes. To prevent excessive absorption, wipe off antigens producing large reactions as soon as the wheal appears. Record the size of the reaction. Delayed reactions may rarely occur from tests, so it may be helpful to examine the test sites in 24 hours.

Use of Scarifiers and Spacing. Make scarifications at least 2.5 cm apart. Use more space between pollen tests to prevent smearing into adjacent sites. Hold the scarifier between the thumb and index finger, press the sharp edge of the instrument against the skin and twirl instrument rapidly. The scratch should disrupt only the outer layers of epidermis but should not produce immediate oozing of blood. The amount of pressure needed to produce a satisfactory scratch will vary between patients according to the thickness or fragility of their skin. Experience will indicate the proper amount of pressure to exert in making the scratch. If the scarifier is kept sharp and the scratch made quickly, discomfort to the patient is minimized.

Use of Prick Test Needles. The skin is cleaned and single drops of each extract applied to the properly identified test sites. A small, sterile disposable needle, such as a 1/2-inch 26 gauge needle (with the bevel up), a bifurcated vaccinating needle, or a Prick Lancetter™ is inserted through the drop superficially into the skin, the skin lifted slightly and the needle withdrawn. No bleeding should be produced. After about 1 minute the extract may be wiped away.

3. Most Satisfactory Sites for Testing
Prior to testing, clean the skin area to be tested with ether or alcohol and allow to dry. Use a sterile instrument for each patient. The back or the volar surface of the arms are the most satisfactory sites for testing. Skin of the posterior thighs or abdomen may be used if necessary. Avoid very hairy areas where possible, since the reactions will be smaller and more difficult to interpret. The most satisfactory areas of the back are from the posterior axillary fold to 2.5 cm from the spinal column, and from the top of the scapula to the lower rib margins. The best areas of the arms are the volar surfaces from the axilla to 2.5 or 5 cm above the wrist, skipping the anti-cubital space.

4. Use of Antigen Mixes
The use of complicated mixes of unrelated pollens for testing is not recommended since in the case of a positive reaction, it does not indicate which pollen(s) are responsible, and, in the case of a negative reaction, it fails to indicate whether the individual pollens at full concentration would give a positive reaction.

5. Reading Skin Test Reactions
A positive reaction consists of an urticarial wheal with surrounding erythema (resembling somewhat a mosquito bite reaction) larger than the control site. The smallest reaction considered positive is erythema with a central papule at least 5 mm in diameter. In some instances with no reaction at the control site, erythema may be considered an indication of sensitivity. In general, the size of wheal and erythema response correlates directly with the patient’s sensitivity to that allergen.

Standardized Products
(a) Mites:
The skin test concentration of 30,000 AU/mL in dropper vials is used for scratch, prick or puncture testing. Puncture tests performed on 12 highly sensitive subjects showed the following:

Species | Mean Sum of Wheal ± Std. Dev. (mm) | Mean Sum of Erythema ± Std. Dev. (mm)
D. farinae | 22.4 ± 10.7 | 82.2 ± 21.7
D. pteronyssinus | 24.0 ± 9.9 | 89.3 ± 24.5

The sum of a skin response is the sum of the longest diameter and the mid-point orthogonal diameter.

(b) Cat Hair and Cat Pelt: The skin test concentration of 10,000 BAU/mL (10-19.9 Fel d 1 Units/mL) in dropper vials is used for prick or puncture testing. Puncture tests performed on 15 highly sensitive subjects showed the following:

Product | Mean Sum of Wheal ± Std. Dev (mm) | Mean Sum of Erythema ± Std. Dev (mm)
Standardized Cat Hair | 15.1 ± 3.8 | 73.3 ± 14.3
Standardized Cat Pelt | 13.9 ± 4.3 | 67.3 ± 13.3

The sum of a skin response is the sum of the longest diameter and the mid-point orthogonal diameter.

(c) Ragweed pollen (Short Ragweed or Giant and Short Ragweed Mixture) Antigen E Assayed: Short Ragweed extract at 1:20 w/v in 50% glycerin containing approximately 100 to 300 units of Amb a 1/mL or Giant and Short Ragweed Mix at 1:20 w/v in 50% glycerin containing approximately 50 to 150 units of Amb a 1/mL are usually used for scratch, prick or puncture testing.
Refer to the following table to determine the skin test sensitivity grade. The corresponding ∑E (sum of the longest diameter and the mid-point orthogonal diameters of erythema) is also presented.

Grade | Erythema mm | Papule or Wheal mm | Corresponding mm ∑E
0 | <5 | <5 | <10
± | 5-10 | 5-10 | 10-20
1+ | 11-20 | 5-10 | 20-40
2+ | 21-30 | 5-10 | 40-60
3+ | 31-40 | 10-15 (a) | 60-80
4+ | >40 | >15 (b) | >80

(a) or with pseudopods (b) or with many pseudopods

A positive skin reaction to any allergen must be interpreted in light of the patient’s history of symptoms, time of the year, and known exposures.

THE SKIN TESTS ARE IN NO WAY A SUBSTITUTE FOR A CAREFUL ALLERGIC HISTORY. THEY SERVE AS ADDITIONAL INFORMATION TO AID IN IDENTIFYING CAUSATIVE ALLERGENS IN PATIENTS WITH ALLERGIC DISORDERS.

6. Geriatric Use

The dose is the same in patients of all age groups. Because the wheal size in response to allergen skin testing decreases with age, appropriate histamine positive control skin tests must be performed.1

7. Pediatric Use

The dose is the same in patients of all age groups. Wheal size in response to allergen skin testing can be smaller in infants than in adults. Appropriate histamine positive control skin tests must be performed.1

HOW SUPPLIED

In 5 mL dropper bottles of extract at 1:10 w/v except pollen at 1:20, AP™ extracts at 1:50 w/v, except AP™ Dog Hair-Dander at 1:100 w/v, AP™ House Dust at 20,000 PNU/mL, some mixes as Concentrate, and Standardized products at AU/mL (Mite extracts at 30,000 AU/mL) or BAU/mL (Cat Hair and Pelt extracts at 10,000 BAU/mL) value. Strengths are listed on product labels.

STORAGE

The expiration date of the diagnostic extracts is listed on the container label. The extract should be stored at 2° - 8°C and kept at this temperature range during office use.

LIMITED WARRANTY

A number of factors beyond our control could reduce the efficacy of this product or even result in an ill effect following its use. These include storage and handling of the product after it leaves our hands, diagnosis, dosage, method of administration, and biological differences in individual patients. Because of these factors, it is important that this product be stored properly, and that the directions be followed carefully during use. No warranty, express or implied, including any warranty of merchantability or fitness, is made. Representatives of the Company are not authorized to vary the terms or the contents of any printed labeling, including the package insert, for this product except by printed notice from the Company’s headquarters. The prescriber and user of this product must accept the terms hereof.

REFERENCES

1. Middleton, Elliott, Jr., C.E. Reed, E.F. Ellis (ed.) Allergy Principles and Practice. Fourth Edition, Vol. 1. C.V. Mosby. 1993.
2. Sheldon, J.M., R.G. Lovell, K.P. Mathews. A Manual of Clinical Allergy. W.B. Saunders. 1967.
3. Tuft, L., H.L. Mueller. Allergy in Children. W.B. Saunders. 1970.
4. DuBuske, L.M., C.J. Ling, A.L. Sheffer. Special problems regarding allergen immunotherapy. Immunol. Allergy Clin. North Am. (USA). 12(1): 145-175, 1992.
5. Weinstein, A.M., B.D. Dubin, W.K. Podleski, S.L. Spector, R.S. Farr. Asthma and pregnancy. JAMA. 124(11): 1161-1165, 1979.
6. Jacobs, Robert L., Geoffrey W. Rake, Jr., et.al. Potentiated anaphylaxis in patients with drug-induced beta-adrenergic blockade. J. Allergy Clin. Immunol. 68(2): 125-127, August 1981.
7. Lockey, Richard F., Linda M. Benedict, Paul C. Turkeltaub, Samuel C. Bukantz. Fatalities from immunotherapy (IT) and skin testing (ST). J. Allergy Clin. Immunol. 79(4): 660-677, 1987.
8. Turkeltaub, Paul C., Peter J. Gergen. The risk of adverse reactions from percutaneous prick-puncture allergen skin testing, venipuncture, and body measurements: Data from the second National Health and Nutrition Examination Survey 1976-80 (NHANES II). J. Allergy Clin. Immunol. 84(6): 886-890, Dec. 1989.
9. Pipkorn, Ulf. Pharmacological influence of anti-allergic medication on In Vivo allergen testing. Allergy. 43: 81-86, 1988.
10. Andersson, M., U. Pipkorn. Inhibition of the dermal immediate allergic reaction through prolonged treatment with topical glucocorticosteroids. J. Allergy Clin. Immunol. 79 (2): 345-349, February 1987.
11. Rao, Kamineni S., et al. Duration of suppressive effect of tricyclic anti-depressants on histamine induced wheal and flare reactions on human skin. J. Allergy Clin. Immunol. 82: 752-757, November 1988.
12. Pipkorn, Ulf, M. Andersson. Topical dermal anesthesia inhibits the flare but not the wheal response to allergen and histamine in the skin prick test. Clin. Allergy. 17: 307-311, 1987.
13. Turkeltaub, Paul C., Suresh, C. Rastogi, Harold Baer. Office of Biologics Research and Review skin test method for evaluation of subject sensitivity to standardized allergenic extracts and for assignment of allergy units to reference preparations using the ID50EAL method (Intradermal Dilution for 50 mm Sum of Erythema Determines the Allergy Unit). Methods of the Allergenic Products Branch Office of Biologics Research and Review, FDA, Bethesda, MD 20892. Revised May 9, 1986.
14. Food and Drug Administration. Biological products; Allergenic extracts classified in Category IIIB; Final order; Revocation of licenses. Federal Register. 59(220): 59228ff, November 16, 1994.